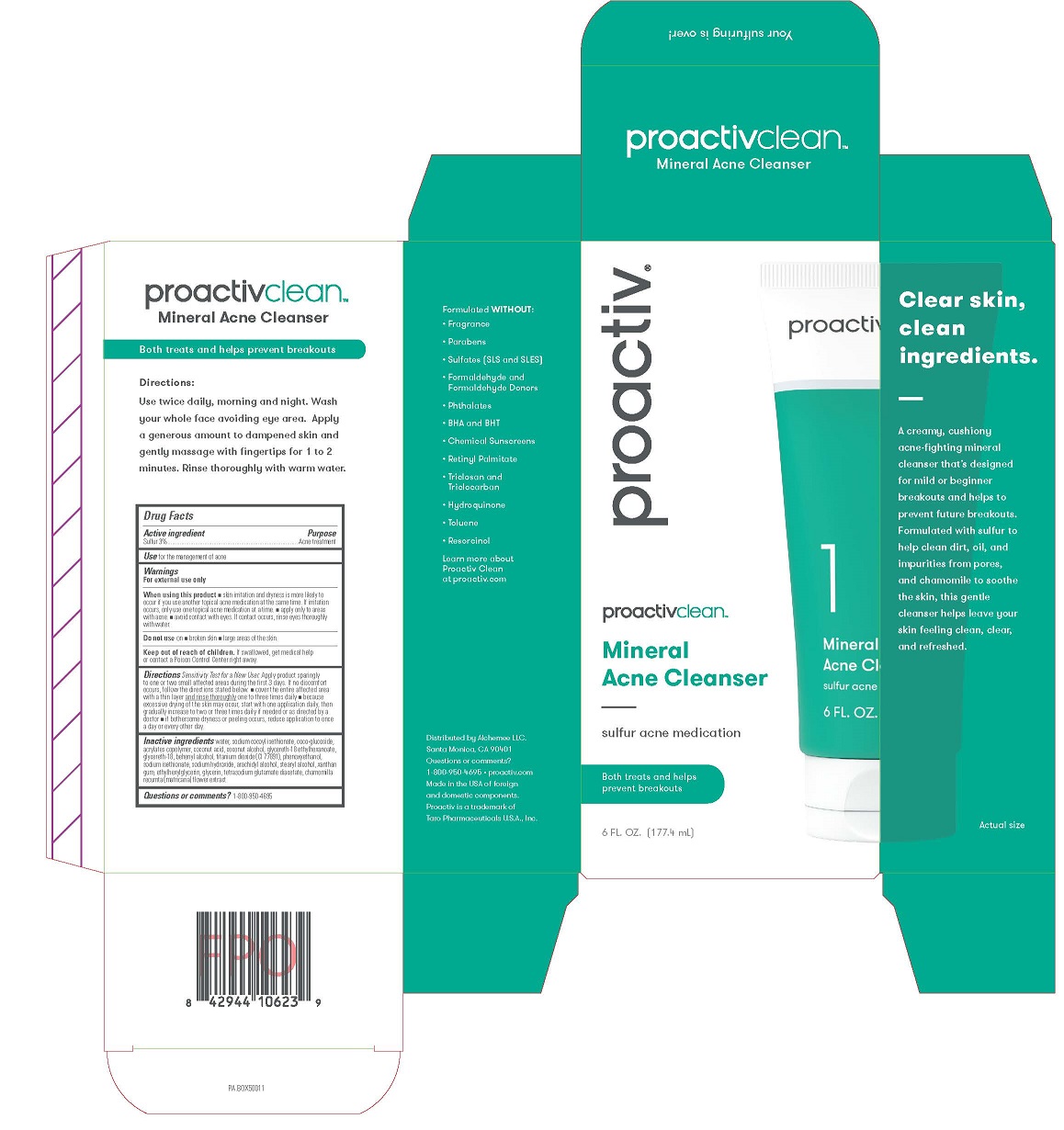 DRUG LABEL: Proactiv Clean Mineral Acne Cleanser
NDC: 11410-457 | Form: CREAM
Manufacturer: Alchemee, LLC
Category: otc | Type: HUMAN OTC DRUG LABEL
Date: 20260107

ACTIVE INGREDIENTS: SULFUR 3 g/100 mL
INACTIVE INGREDIENTS: WATER; SODIUM COCOYL ISETHIONATE; COCO GLUCOSIDE; COCONUT ACID; COCONUT ALCOHOL; GLYCERETH-18 ETHYLHEXANOATE; GLYCERETH-18; DOCOSANOL; TITANIUM DIOXIDE; PHENOXYETHANOL; SODIUM ISETHIONATE; SODIUM HYDROXIDE; ARACHIDYL ALCOHOL; STEARYL ALCOHOL; XANTHAN GUM; ETHYLHEXYLGLYCERIN; GLYCERIN; TETRASODIUM GLUTAMATE DIACETATE; MATRICARIA CHAMOMILLA

Proactiv®Clean Mineral Acne Cleanser

Drug Facts

Active ingredient

Sulfur 3%

Purpose

Acne treatment

Use

for the management of acne

Warnings

For external use only

When using this product

- skin irritation and dryness is more likely to occur if you use another topical acne medication at the same time. If irritation occurs, only use one topical acne medication at a time.
- apply only to areas with acne.
- avoid contact with eyes. If contact occurs, rinse eyes thoroughly with water.

Do not useon

- broken skin
- large areas of the skin.

Keep out of reach of children.

If swallowed, get medical help or contact a Poison Control Center right away.

Directions

- Sensitivity Test for a New User. Apply product sparingly to one or two small affected areas during the first 3 days. If no discomfort occurs, follows the directions stated below.
- cover the entire affected area with a thin layer and rinse thoroughly one to three times daily
- because excessive drying of the skin may occur, start with one application daily, then gradually increase to two or three times daily if needed or as directed by a doctor
- if bothersome dryness or peeling occurs, reduce application to once a day or every other day.

Inactive ingredients

water, sodium cocoyl isethionate, coco-glucoside, acrylates copolymer, coconut acid, coconut alcohol, glycereth-18 ethylhexanoate, glycereth-18, behenyl alcohol, titanium dioxide (CI 77891), phenoxyethanol, sodium isethionate, sodium hydroxide, arachidyl alcohol, stearyl alcohol, xanthan gum, ethylhexylglycerin, glycerin, tetrasodium glutamate diacetate, chamomilla recumta (matricaria) flower extract

Questions or comments?

Within US 1-800-950-4695

Distributed by Alchemee LLC.
Santa Monica, CA 90401
Questions or comments?
1-800-950-4695 • proactiv.com
Made in the USA of foreign and domestic components.
Proactiv is a trademark of Taro Pharmaceuticals U.S.A., Inc.

PRINCIPAL DISPLAY PANEL - 6 FL. OZ. (177.4 mL)

proactivcleanTM

Mineral
Acne Cleanser
sulfur acne medication
Both treats and helps
prevent breakouts